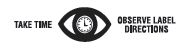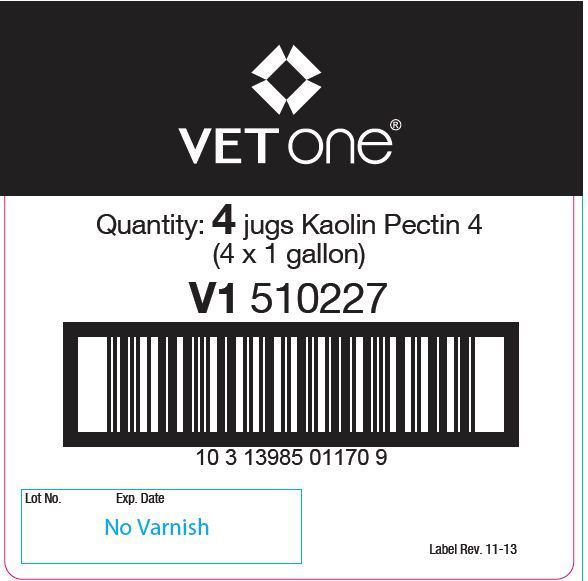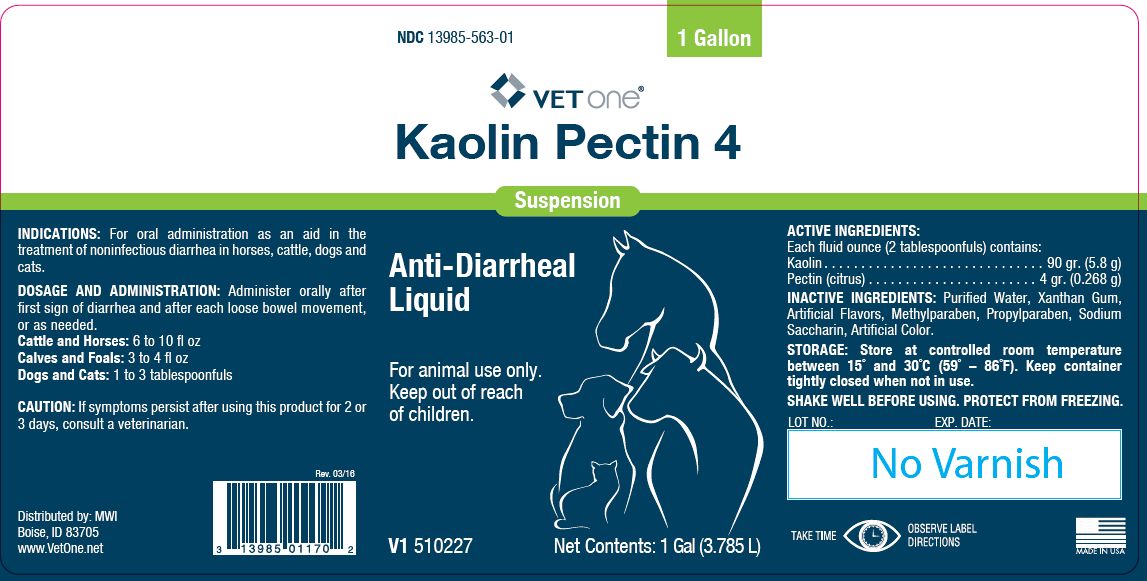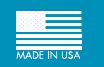 DRUG LABEL: Kaolin Pectin 4
NDC: 13985-563 | Form: SUSPENSION
Manufacturer: MWI/Vet One
Category: animal | Type: OTC ANIMAL DRUG LABEL
Date: 20161116

ACTIVE INGREDIENTS: KAOLIN 208.1 g/1 L; PECTIN, CITRUS 8.8 g/1 L

Kaolin Pectin 4

PURPOSE

Suspension

Anti-Diarrheal Liquid

KEEP OUT OF REACH OF CHILDREN

For animal use only.
Keep out of reach of children.

INDICATIONS:

For oral administration as an aid in the treatment of noninfectious diarrhea in horses, cattle, dogs and cats.

DOSAGE AND ADMINISTRATION:

Administer orally after first sign of diarrhea and after each loose bowel movement, or as needed.
Cattle and Horses: 6 to 10 fl oz
Calves and Foals: 3 to 4 fl oz
Dogs and Cats: 1 to 3 tablespoonfuls

CAUTION:

If symptoms persist after using this product for 2 or 3 days, consult a veterinarian.

ACTIVE INGREDIENTS:

Each fluid ounce (2 tablespoonfuls) contains:
Kaolin . . . . . . . . . . . . . . . . . . . . . . . . . . . . . . 90 gr. (5.8 g)
Pectin (citrus) . . . . . . . . . . . . . . . . . . . . . . . 4 gr. (0.268 g)

INACTIVE INGREDIENTS:

Purified Water, Xanthan Gum, Artificial Flavors, Methylparaben, Propylparaben, Sodium Saccharin, Artificial Color.

STORAGE:

Store at controlled room temperature between 15° and 30°C (59° – 86°F). Keep container tightly closed when not in use.
SHAKE WELL BEFORE USING. PROTECT FROM FREEZING.

Net Contents:

1 Gal (3.785 L) V1 510227

INFORMATION FOR OWNERS/CAREGIVERS

Distributed by: MWI
Boise, ID 83705
www.VetOne.net